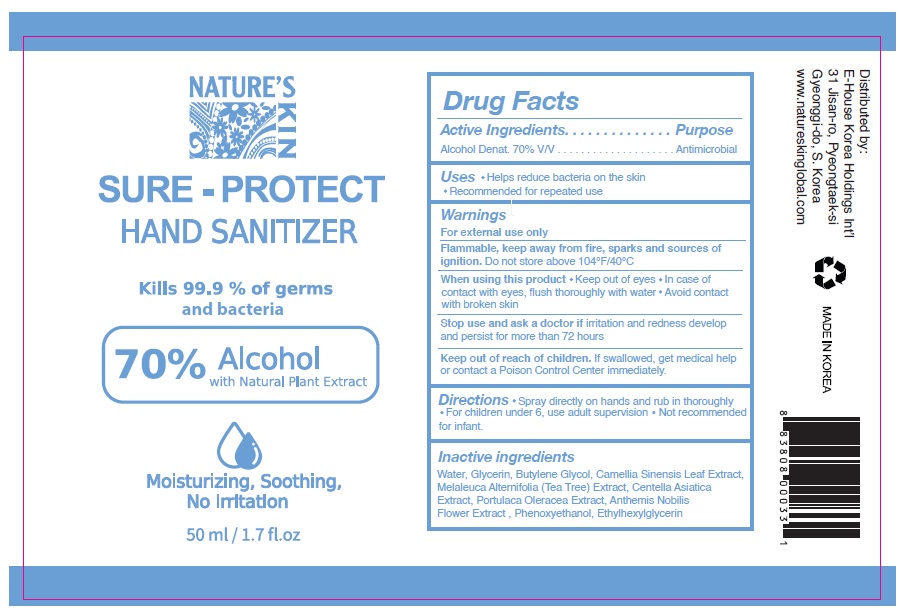 DRUG LABEL: SURE PROTECT HAND SANITIZER
NDC: 50387-002 | Form: LIQUID
Manufacturer: E-House Korea Holdings International
Category: otc | Type: HUMAN OTC DRUG LABEL
Date: 20200916

ACTIVE INGREDIENTS: ALCOHOL 70 mL/100 mL
INACTIVE INGREDIENTS: WATER; GLYCERIN; BUTYLENE GLYCOL; GREEN TEA LEAF; MELALEUCA ALTERNIFOLIA LEAF; CENTELLA ASIATICA WHOLE; PURSLANE; CHAMAEMELUM NOBILE FLOWER; PHENOXYETHANOL; ETHYLHEXYLGLYCERIN

Active Ingredient

Alcohol Denat. 70 %v/v

Purpose

Antimicrobial

Use

- Helps reduce bacteria on the skin.
- Recommended for repeated use.

Warnings

For external use only.

Flammable, keep away from fire, sparks and sources of ignition. Do not store above 104°F/40°C

When using this product

- keep out of eyes. In case of contact with eyes, flush thoroughly with water.
- Avoid contact with broken skin.

Stop use and ask a doctor if irritation and redness develop and persist for more than 72 hours.

Keep out of reach of children. If swallowed, get medical help or contact a Poison Control Center immediately.

Directions

- Spray directly on hands and rub in thoroughly. For children under 6, use
- adult supervision. Not recommended for infant.

Inactive ingredients

Water, Glycerin, Butylene Glycol, Camellia Sinensis Leaf Extract, Melaleuca Alternifolia (Tea Tree) Extract, Centella Asiatica Extract, Portulaca Oleracea Extract, Anthemis Nobilis Flower Extract , Phenoxyethanol, Ethylhexylglycerin